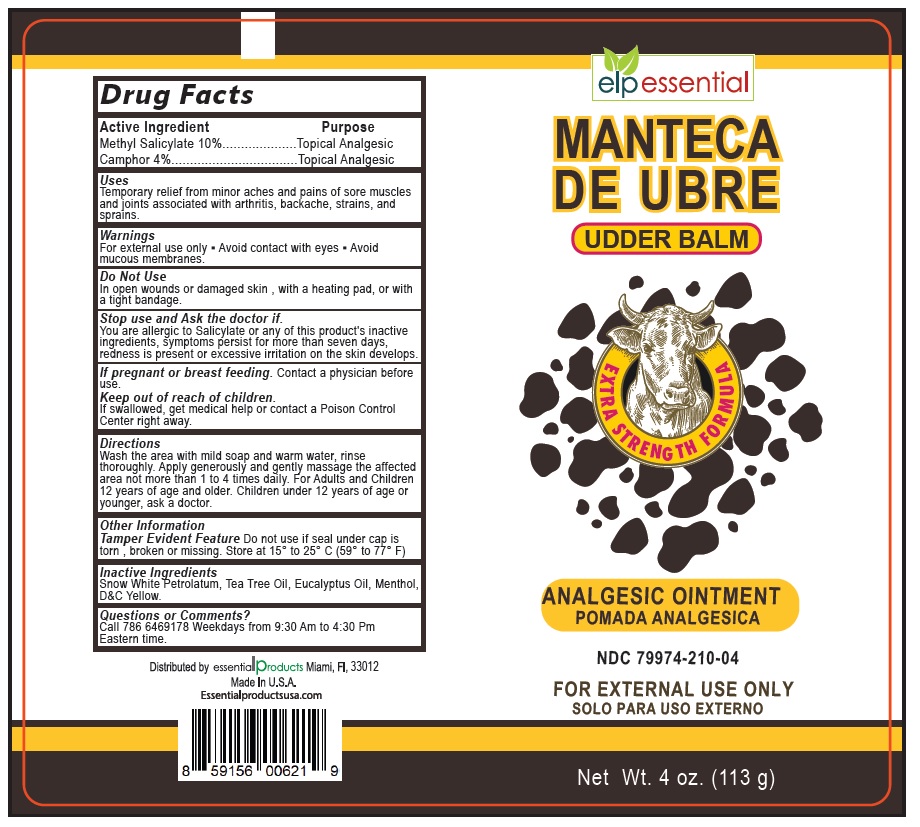 DRUG LABEL: elp essential MANTECA DE UBRE
NDC: 79974-210 | Form: OINTMENT
Manufacturer: Miramar Cosmetics, Inc DBA Miramar Lab
Category: otc | Type: HUMAN OTC DRUG LABEL
Date: 20250113

ACTIVE INGREDIENTS: METHYL SALICYLATE 10 g/100 g; CAMPHOR (NATURAL) 4 g/100 g
INACTIVE INGREDIENTS: WHITE PETROLATUM; TEA TREE OIL; EUCALYPTUS OIL; MENTHOL, UNSPECIFIED FORM; D&C YELLOW NO. 10

elp essential MANTECA DE UBRE

Active Ingredient

Methyl Salicylate 10%

Camphor 4%

Purpose

Topical Analgesic

Uses

Temporary relief from minor aches and pains of sore muscles and joints associated with arthritis, backache, strains, and sprains.

Warnings

For external use only • Avoid contact with eyes • Avoid mucous membranes

Do Not Use
In open wounds or damaged skin, with a heating pad, or with a tight bandage.

Stop use and Ask the doctor if.
You are allergic to Salicylate or any of this product's inactive ingredients, symptoms persist for more than seven days, redness is present or excessive irritation on the skin develops.

If pregnant or breast feeding. Contact a physician before use.

Keep out of reach of children.
If swallowed, get medical help or contact a Poison Control Center right away.

Directions

Wash the area with mild soap and warm water, rinse thoroughly. Apply generously and gently massage the affected area not more than 1 to 4 times daily. For Adults and Children 12 years of age and older. Children under 12 years of age or younger, ask a doctor.

Other Information

Tamper Evident Feature Do not use if seal under cap is torn, broken or missing. Store at 15° to 25° C (59° to 77° F)

Inactive Ingredients

Snow White Petrolatum, Tea Tree Oil, Eucalyptus Oil, Menthol, D&C Yellow.

Questions or Comments?

Call 786 6469178 Weekdays from 9:30 Am to 4:30 Pm Eastern time.

UDDER BALM

EXTRA STRENGTH FORMULA

ANALGESIC OINTMENT

Distributed by essential products Miami, FL, 33012

Made In U.S.A.

Essentialproductsusa.com